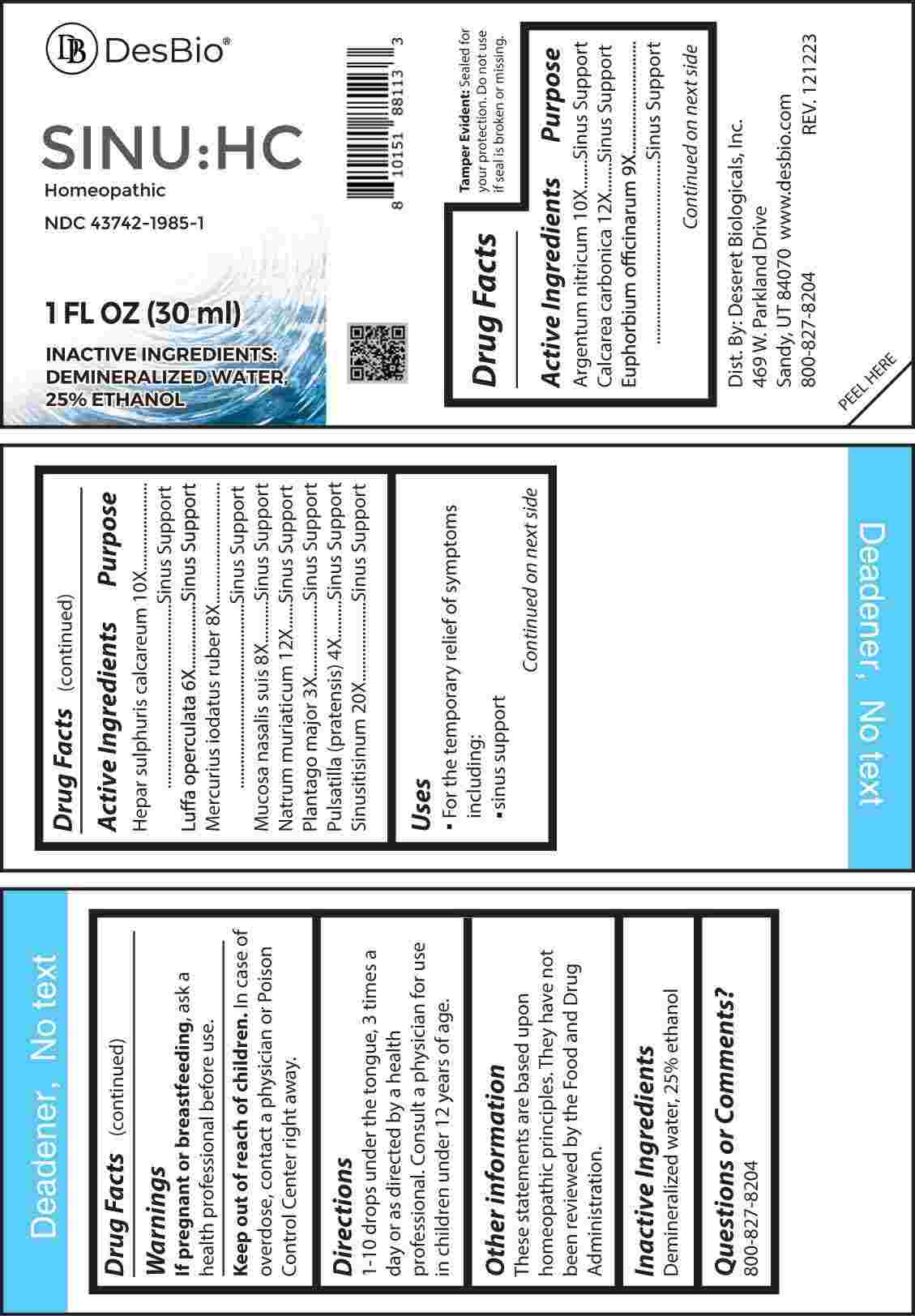 DRUG LABEL: SINU HC
NDC: 43742-1985 | Form: LIQUID
Manufacturer: Deseret Biologicals, Inc.
Category: homeopathic | Type: HUMAN OTC DRUG LABEL
Date: 20240402

ACTIVE INGREDIENTS: PLANTAGO MAJOR WHOLE 3 [hp_X]/1 mL; PULSATILLA PRATENSIS WHOLE 4 [hp_X]/1 mL; LUFFA OPERCULATA FRUIT 6 [hp_X]/1 mL; MERCURIC IODIDE 8 [hp_X]/1 mL; SUS SCROFA NASAL MUCOSA 8 [hp_X]/1 mL; EUPHORBIA RESINIFERA RESIN 9 [hp_X]/1 mL; SILVER NITRATE 10 [hp_X]/1 mL; CALCIUM SULFIDE 10 [hp_X]/1 mL; OYSTER SHELL CALCIUM CARBONATE, CRUDE 12 [hp_X]/1 mL; SODIUM CHLORIDE 12 [hp_X]/1 mL; SINUSITISINUM 20 [hp_X]/1 mL
INACTIVE INGREDIENTS: WATER; ALCOHOL

DRUG FACTS:

ACTIVE INGREDIENTS:

Argentum Nitricum 10X, Calcarea Carbonica 12X, Euphorbium Officinarum 9X, Hepar Sulphuris Calcareum 10X, Luffa Operculata 6X, Mercurius Iodatus Ruber 8X, Mucosa Nasalis Suis 8X, Natrum Muriaticum 12X, Plantago Major 3X, Pulsatilla (Pratensis) 4X, Sinusitisinum 20X.

PURPOSE:

Argentum Nitricum – Sinus Support, Calcarea Carbonica - Sinus Support, Euphorbium Officinarum - Sinus Support, Hepar Sulphuris Calcareum - Sinus Support, Luffa Operculata - Sinus Support, Mercurius Iodatus Ruber - Sinus Support, Mucosa Nasalis Suis - Sinus Support, Natrum Muriaticum - Sinus Support, Plantago Major - Sinus Support, Pulsatilla (Pratensis) - Sinus Support, Sinusitisinum - Sinus Support

USES:

• For the temporary relief of symptoms including:

• sinus support

These statements are based upon homeopathic principles. They have not been reviewed by the Food and Drug Administration.

WARNINGS:

If pregnant or breast-feeding, ask a health professional before use.

Keep out of reach of children. In case of overdose, contact a physician or Poison Control Center right away.

Tamper Evident: Sealed for your protection. Do not use if seal is broken or missing.

KEEP OUT OF REACH OF CHILDREN:

In case of overdose, contact a physician or Poison Control Center right away.

DIRECTIONS:

1-10 drops under the tongue, 3 times a day or as directed by a health professional. Consult a physician for use in children under 12 years of age.

INACTIVE INGREDIENTS:

Demineralized water, 25% ethanol

QUESTIONS:

Dist. By: Deseret Biologicals, Inc.

469 W. Parkland Drive

Sandy, UT 84070

www.desbio.com

800-827-8204

PACKAGE LABEL DISPLAY:

Des Bio

SINU:HC

Homeopathic

NDC 43742-1985-1

1 FL OZ (30 ml)